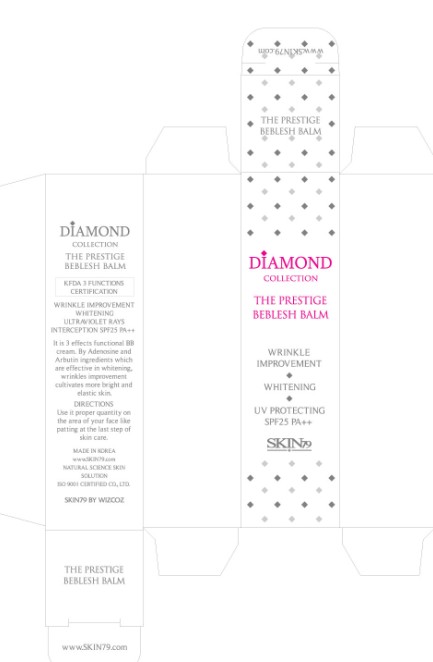 DRUG LABEL: SKIN 79 The Prestige Beblesh Balm (5g)
NDC: 49715-004 | Form: CREAM
Manufacturer: WIZCOZ CORPORATION LTD
Category: otc | Type: HUMAN OTC DRUG LABEL
Date: 20091109

ACTIVE INGREDIENTS: ZINC OXIDE 0.19 g/5 g; TITANIUM DIOXIDE 0.312 g/5 g
INACTIVE INGREDIENTS: DIMETHICONE 0.175 g/5 g; ALUMINUM HYDROXIDE 0.025 g/5 g

ACTIVE INGREDIENT

INGREDIENTS:
WATER, TITANIUM DIOXIDE, CYCLOPENTASILOXANE, PHENYL TRIMETHICONE, BUTYLENE GLYCOL, BUTYLENE GLYCOL DICAPRYLATE/DICAPRATE, ZINC OXIDE, DIMETHICONE, C12-15 ALKYL BENZOATE, CETYL PEG/PPG-10/1 DIMETHICONE, HYDROGENATED POLYDECENE, ARBUTIN, HEXYL LAURATE, POLYGLYCERYL-4 ISOSTEARATE, SORBITAN ISOSTEARATE, NATTO GUM, GLYCERIN, MICA, CYCLOHEXASILOXANE, TALC, SORBITAN OLIVATE, OZOKERITE, DIMETHICONE/VINYL DIMETHICONE CROSSPOLYMER, SODIUM CHLORIDE, DISTEARDIMONIUM HECTORITE, ALUMINUM HYDROXIDE, STEARIC ACID, TRIEHOXYCAPRYLSILANE, DIMETHICONE/METHICONE COPOLYMER, CALCIUM STEARATE, PROPYLENE CARBONATE, TOCOPHEROL ACETATE, HUMAN OLIGOPEPTIDE-1, ALOE BARBADENSIS LEAF JUICE, HYDROLIZED COLLAGE, NELUMBIUM SPECIOSUM FLOWER EXTRACT, CAVIAR EXTRACT, UBIQUINONE, PORTULACA OLERACEA EXTRACT, CAMELLIA SINENSIS LEAF EXTRACT, ACETYL HEXAPEPTIDE-8, ADENOSINE, DISODIUM EDTA, ASPARAGUS LUCIDUS ROOT EXTRACT, TUSSILAGO FARFARA (COLTSFOOT) FLOWER EXTRACT, LAMINARIA JAPONICA EXTRACT, DIAMOND POWDER, AMETHYST POWDER, PEARL POWDER, CORAL POWDER, TOURMALIN, CERAMIDE 3, GOLD, HESPERIDIN METHYL CHALCONE, STEARETH-20, DIPEPTIDE-2, PALMITOYL TETRAPEPTIDE-7, COPPER TRIPEPTIDE-1, LECITHIN, DEA-CETYL PHOSPHATE, RETINYL PALMITATE, SUCROSE DISTEARATE, SODIUM ASCORBYL PHOSPHATE, PANTHENOL, SILK AMINO ACIDES, ASCORBIN ACID, METHYLPARABEN, BUTYLPARABEN, PROPYLPARABEN, FRAGRANCE, IRON OXIDE RED, IRON OXIDE YELLOW, IRON OXIDE BLACK

DIRECTIONS:

Use it proper quantity on the area of your face like patting at the last step of skin care.